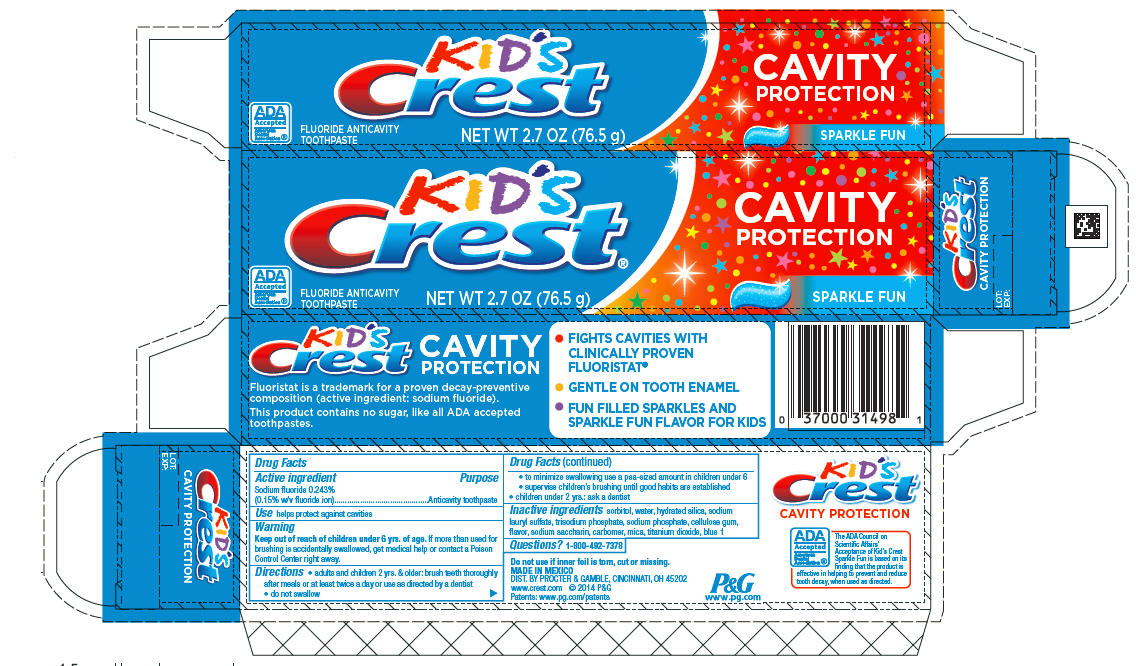 DRUG LABEL: Kids Crest Cavity Protection
NDC: 58933-049 | Form: PASTE, DENTIFRICE
Manufacturer: Procter & Gamble Manufactura, S. de R.L. de C.V.
Category: otc | Type: HUMAN OTC DRUG LABEL
Date: 20251217

ACTIVE INGREDIENTS: SODIUM FLUORIDE 1.5 mg/1 g
INACTIVE INGREDIENTS: HYDRATED SILICA; SODIUM LAURYL SULFATE; SODIUM PHOSPHATE; CARBOXYMETHYLCELLULOSE SODIUM; SACCHARIN SODIUM; MICA; TITANIUM DIOXIDE; WATER; FD&C BLUE NO. 1; SORBITOL

Kid's Crest® Cavity Protection
Sparkle Fun

Active ingredient

Sodium fluoride 0.243%
(0.15% w/v fluoride ion)

Purpose

Anticavity toothpaste

Use

helps protect against cavities

WARNINGS

Warning

Keep out of reach of children under 6 yrs. of age. If more than used for brushing is accidentally swallowed, get medical help or contact a Poison Control Center right away.

Directions

- adults and children 2 yrs. & older: brush teeth thoroughly after meals or at least twice a day or use as directed by a dentist
- do not swallow
- to minimize swallowing use a pea-sized amount in children under 6
- supervise children’s brushing until good habits are established
- children under 2 yrs.: ask a dentist

Inactive ingredients

sorbitol, water, hydrated silica, sodium lauryl sulfate, trisodium phosphate, sodium phosphate, cellulose gum, flavor, sodium saccharin, carbomer, mica, titanium dioxide, blue 1

Questions?

1-800-492-7378

MADE IN MEXICO
DIST. BY PROCTER & GAMBLE, CINCINNATI, OH 45202

PRINCIPAL DISPLAY PANEL - 76.5 g Tube in Carton Label

KID'S
CREST ®

CAVITY
PROTECTION

SPARKLE FUN

ADA
Accepted
American
Dental
Association ®

FLUORIDE
ANTICAVITY
TOOTHPASTE

NET WT 2.7 OZ (76.5 g)